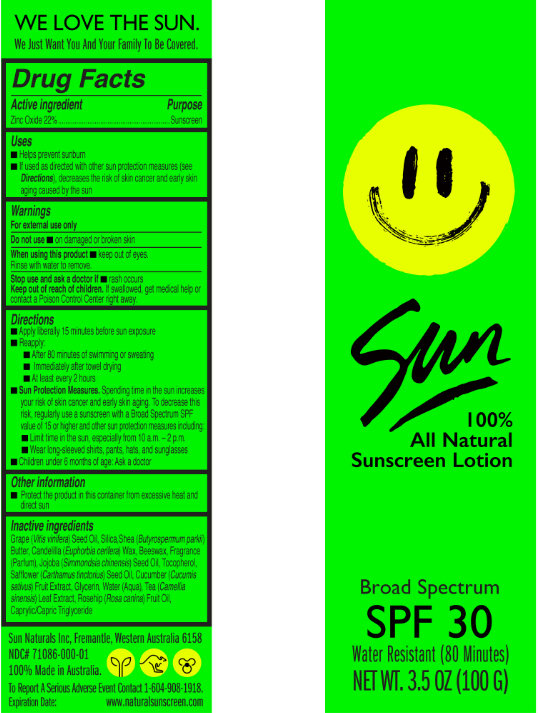 DRUG LABEL: Sun Natural Sunscreen
NDC: 71086-000 | Form: CREAM
Manufacturer: Sun Naturals Inc
Category: otc | Type: HUMAN OTC DRUG LABEL
Date: 20161118

ACTIVE INGREDIENTS: ZINC OXIDE 220 mg/1 g
INACTIVE INGREDIENTS: SHEA BUTTER; SILICON DIOXIDE; CANDELILLA WAX; YELLOW WAX; JOJOBA OIL; TOCOPHEROL; GLYCERIN; WATER; TEA LEAF; ROSA CANINA FRUIT; MEDIUM-CHAIN TRIGLYCERIDES; GRAPE SEED OIL

Sun Natural Sunscreen

Active ingredient

Zinc Oxide 22%

Purpose

Sunscreen

Uses

- Helps prevent sunburn
- If used as directed with other sun protection measures (see Directions), decreases the risk of skin cancer and early skin aging caused by the sun

Warnings

For external use only

Do not use

- on damaged or broken skin

When using this product

- keep out of eyes. Rinse with water to remove.

Stop use and ask a doctor if

- rash occurs

Keep out of reach of children.

If swallowed, get medical help or contact a Poison Control Center right away.

Directions

- Apply liberally 15 minutes before sun exposure
- Reapply:
- After 80 minutes of swimming or sweating
- Immediately after towel drying
- At least every 2 hours
- Sun Protection Measures. Spending time in the sun increases your risk of skin cancer and early skin aging. To decrease this risk, regularly use a sunscreen with a Broad Spectrum SPF value of 15 or higher and other sun protection measures including:
- Limit time in the sun, especially from 10 a.m. – 2 p.m.
- Wear long-sleeved shirts, pants, hats, and sunglasses
- Children under 6 months of age: Ask a doctor

Other information

- Protect the product in this container from excessive heat and direct sun

Inactive ingredients

Caprylic/Capric Triglyceride, Grape (Vitis vinifera) Seed Oil, Silica, Shea (Butyrospermum parkii) Butter, Candelilla (Euphorbia cerifera) Wax, Beeswax, Fragrance (Parfum), Jojoba (Simmondsia chinensis) Seed Oil, Tocopherol, Safflower (Carthamus tinctorius) Seed Oil, Cucumber (Cucumis sativus) Fruit Extract, Glycerin, Water (Aqua), Tea (Camellia sinensis) Leaf Extract, Rosehip (Rosa canina) Fruit Oil